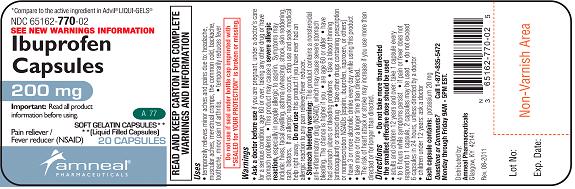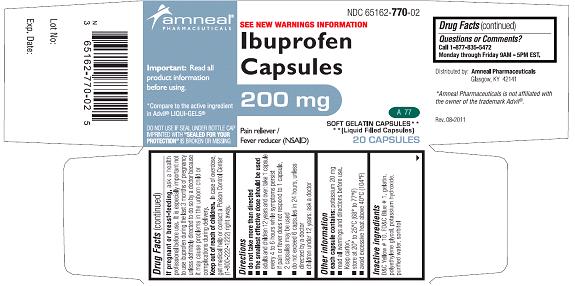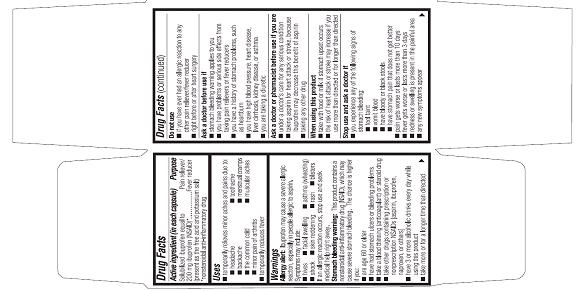 DRUG LABEL: Ibuprofen Pain Reliever/Fever Reducer
NDC: 65162-770 | Form: CAPSULE, LIQUID FILLED
Manufacturer: Amneal Pharmaceuticals LLC
Category: otc | Type: HUMAN OTC DRUG LABEL
Date: 20241025

ACTIVE INGREDIENTS: IBUPROFEN 200 mg/1 1
INACTIVE INGREDIENTS: D&C YELLOW NO. 10; FD&C BLUE NO. 1; GELATIN; POLYETHYLENE GLYCOL, UNSPECIFIED; WATER; POTASSIUM HYDROXIDE; SORBITOL

Ibuprofen Capsules, liquid filled, 200 mg

OTC - ACTIVE INGREDIENT

(in each capsule)

Solubilized ibuprofen equal to 200 mg ibuprofen (NSAID)*

(present as the free acid and potassium salt)

* nonsteroidal anti-inflammatory drug

OTC - PURPOSE

Pain reliever/Fever reducer

INDICATIONS AND USAGE

- temporarily relieves minor aches and pains due to:
- headache
- toothache
- backache
- menstrual cramps
- the common cold
- muscular aches
- minor pain of arthritis
- temporarily reduces fever

WARNINGS

Allergy Alert:

Ibuprofen may cause a severe allergic reaction, especially in people allergic to aspirin. Symptoms may include:

- hives
- facial swelling
- asthma (wheezing)
- shock
- skin reddening
- rash
- blisters

If an allergic reaction occurs, stop use and seek medical help right away.

Stomach Bleeding warning:

This product contains a nonsteroidal anti-inflammatory drug (NSAID), which may cause severe stomach bleeding. The chance is higher if you:

- are age 60 or older
- have had stomach ulcers or bleeding problems
- take a blood thinning (anticoagulant) or steroid drug
- take other drugs containing prescription or nonprescription NSAIDs [aspirin, ibuprofen, naproxen, or others]
- have 3 or more alcoholic drinks every day while using this product
- take more or for a longer time than directed

OTC - DO NOT USE

Do not use

- if you have ever had an allergic reaction to any other pain reliever/fever reducer
- right before or after heart surgery

OTC - ASK DOCTOR

Ask a doctor before use if

- stomach bleeding warning applies to you
- you have problems or serious side effects from taking pain relievers or fever reducers
- you have a history of stomach problems, such as heartburn
- you have high blood pressure, heart disease, liver cirrhosis, kidney disease, or asthma
- you are taking a diuretic

OTC - ASK DOCTOR/PHARMACIST

Ask a doctor or pharmacist before use if you are

- under a doctor’s care for any serious condition
- taking aspirin for heart attack or stroke, because ibuprofen may decrease this benefit of aspirin
- taking any other drug

OTC - WHEN USING

When using this product

- take with food or milk if upset stomach occurs
- the risk of heart attack or stroke may increase if you use more than directed or for longer than directed

OTC - STOP USE

Stop use and ask a doctor if

- you experience any of the follwing signs of stomach bleeding:
- feel faint
- vomit blood
- have bloody or black stools
- have stomach pain that does not get better
- pain gets worse or lasts more than 10 days
- fever gets worse or lasts more than 3 days
- redness or swelling is present in the painful area
- any new symptoms appear

OTC - PREGNANCY OR BREAST FEEDING

If pregnant or breast-feeding

Ask a health professional before use. It is especially important not to use ibuprofen during the last 3 months of pregnancy unless definitely directed to do so by a doctor because it may cause problems in the unborn child or complications during delivery.

OTC - KEEP OUT OF REACH OF CHILDREN

Keep out of reach of children.

In case of overdose, get medical help or contact a Poison Control Center (1-800-222-1222) right away.

DOSAGE AND ADMINISTRATION

DIRECTIONS

- do not take more than directed
- the smallest effective dose should be used
- adults and children 12 years and over: take 1 capsule every 4 to 6 hours while symptoms persist
- if pain or fever does not respond to 1 capsule, 2 capsules may be used.
- do not exceed 6 capsules in 24 hours, unless directed by a doctor
- children under 12 years: ask a doctor

OTHER INFORMATION

- each capsule contains: potassium 20 mg
- read all warnings and directions before use. Keep carton.
- Store at 20º to 25ºC (68º to 77ºF)
- avoid excessive heat above 40ºC (104ºF)

INACTIVE INGREDIENTS

D&C Yellow # 10, FD&C Blue # 1, gelatin, polyethylene glycol, potassium hydroxide, purified water, sorbitol

OTC – QUESTIONS OR COMMENTS?

Call 1-877-835-5472 Monday through Friday 9AM - 5PM EST

READ AND KEEP CARTON FOR COMPLETE WARNINGS AND INFORMATION

Do Not Use if printed foil under cap is broken or missing.

Distributed by: Amneal Pharmaceuticals

Glasgow, KY 42141

Rev. 08-2011